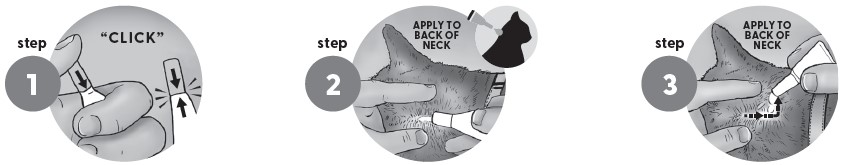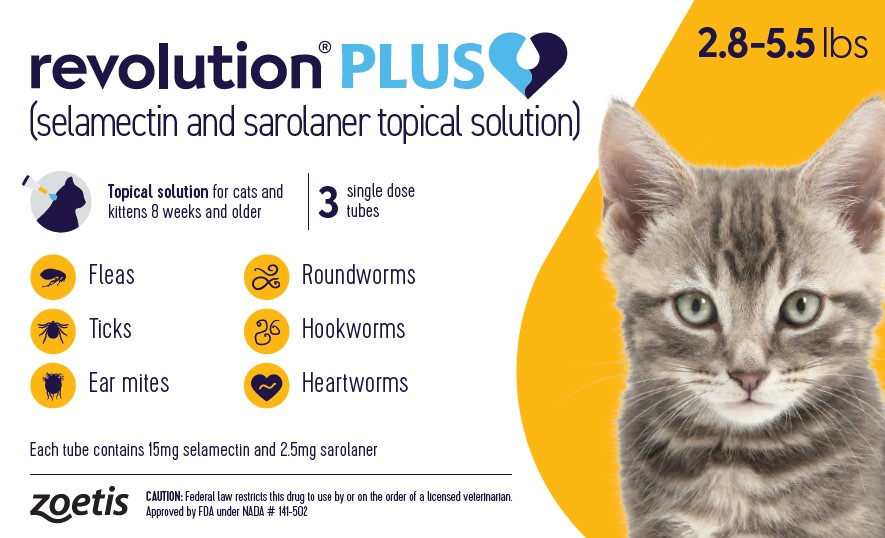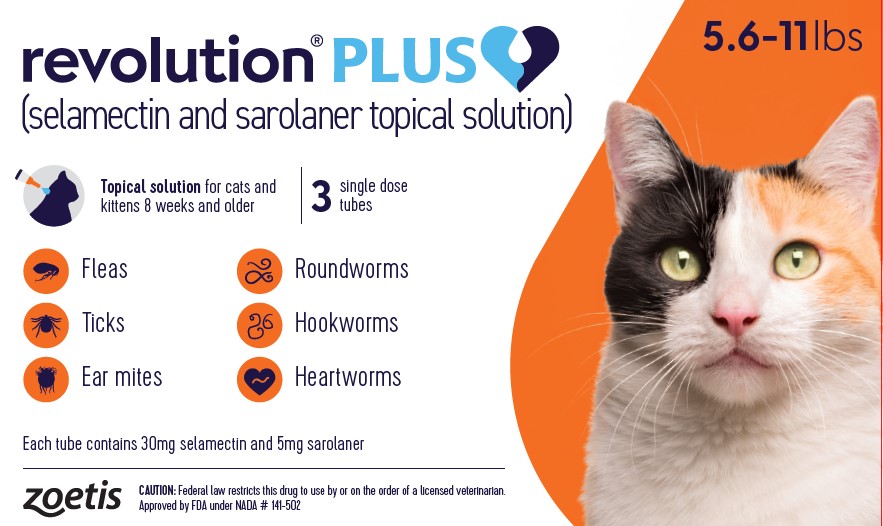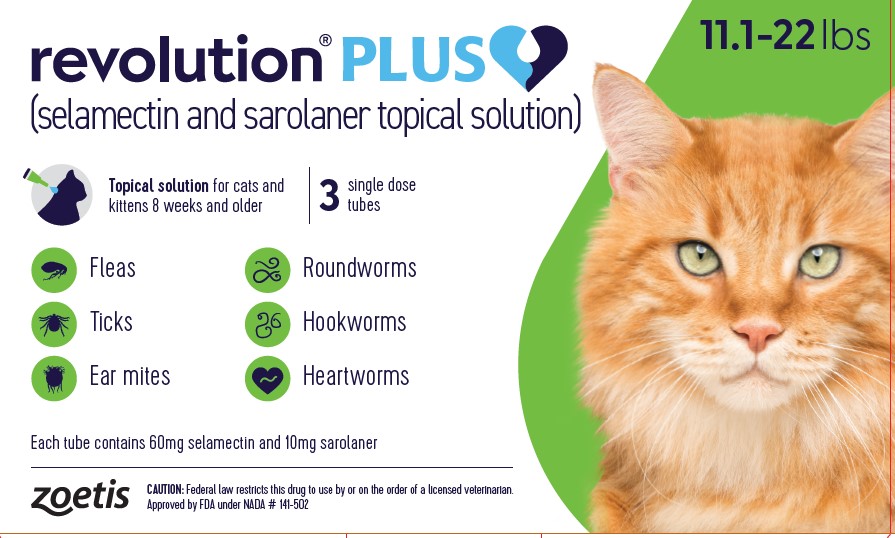 DRUG LABEL: REVOLUTION PLUS
NDC: 54771-0411 | Form: SOLUTION
Manufacturer: Zoetis Inc.
Category: animal | Type: PRESCRIPTION ANIMAL DRUG LABEL
Date: 20241212

ACTIVE INGREDIENTS: SAROLANER 10 mg/1 mL; SELAMECTIN 60 mg/1 mL

revolution® PLUS

revolution® PLUS
(selamectin and sarolaner topical solution)

CAUTION:

Federal law restricts this drug to use by or on the order of a licensed veterinarian.

DESCRIPTION:

REVOLUTION PLUS (selamectin and sarolaner topical solution) for Cats is available as a colorless to yellow, ready to use solution in single dose tubes for topical (dermal) treatment of cats and kittens eight weeks of age and older. The content of each tube is formulated to provide a minimum of 2.7 mg/lb (6 mg/kg) of body weight of selamectin and 0.45 mg/lb (1.0 mg/kg) of body weight of sarolaner. Inactive ingredients: Dipropylene Glycol Monomethylether, Isopropyl Alcohol, Butylated Hydroxytoluene.

Selamectin is a member of the macrocyclic lactone class of parasiticides and the chemical name is 25-Cyclohexyl-4’-O-de(2,6-dideoxy-3-O-methyl-α-l-arabino-hexopyranosyl)-5-demethoxy-25-de(1-methylpropyl)-22,23-dihydro-5-(hydroxyimino)-avermectin A1a.

Sarolaner is a member of the isoxazoline class of parasiticides and the chemical name is 1(5’-((5S)-5-(3,5-Dichloro-4-fluorophenyl)-5-(trifluoromethyl)-4,5-dihydroisoxazol-3-yl)-3’-H-spiro(azetidine-3,1’-(2)benzofuran)-1-yl)-2-(methylsulfonyl)ethanone. REVOLUTION PLUS contains the S-enantiomer of sarolaner.

INDICATIONS:

REVOLUTION PLUS is indicated for the prevention of heartworm disease caused by Dirofilaria immitis, the treatment and control of roundworm (Toxocara cati) and intestinal hookworm (Ancylostoma tubaeforme) infections, and the treatment and control of ear mite (Otodectes cynotis) infestations.
REVOLUTION PLUS kills adult fleas (Ctenocephalides felis) and is indicated for the treatment and prevention of flea infestations, the prevention of Dipylidium caninum (tapeworm) infections as a direct result of killing Ctenocephalides felis vector fleas on the treated cat, and the treatment and control of tick infestations with Amblyomma americanum (lone star tick), Amblyomma maculatum (Gulf Coast tick), Dermacentor variabilis (American dog tick), and Ixodes scapularis (black-legged tick) for one month in cats and kittens 8 weeks and older, and weighing 2.8 pounds or greater.

DOSAGE AND ADMINISTRATION:

The recommended minimum dosage is 2.7 mg selamectin per pound (6 mg/kg) of body weight and 0.45 mg sarolaner per pound (1 mg/kg) of body weight.

Administer the entire contents of a single tube (or two tubes in combination for cats weighing over 22 pounds) of REVOLUTION PLUS topically in accordance with the following table.

Body Weight (lbs) | Tube Cap Color | Tube Volume (mL) | Tube Contents
Body Weight (lbs) | Tube Cap Color | Tube Volume (mL) | Selamectin; (mg/tube) | Sarolaner; (mg/tube)
2.8 - 5.5 | gold | 0.25 | 15 | 2.5
5.6 - 11 | orange | 0.5 | 30 | 5
11.1 - 22* | green | 1 | 60 | 10

* Cats over 22 lbs should be treated with the appropriate combination of tubes.
Recommended for use in cats and kittens 8 weeks of age or older.

A veterinarian or veterinary technician should demonstrate or instruct the pet owner regarding the appropriate technique for applying REVOLUTION PLUS topically to cats and kittens prior to first use.

Firmly press the cap down to puncture the seal on the REVOLUTION PLUS tube; a clicking sound will confirm that the cap has successfully punctured the seal. Remove the cap and check to ensure that the tip of the tube is open. To administer the product, part the hair on the back of the animal at the base of the neck in front of the shoulder blades until the skin is visible. Place the tip of the tube on the skin and squeeze the tube 3 or 4 times to empty its entire contents directly on to the skin in one spot. Keeping the tube squeezed, drag it away from the liquid and lift to remove. Check the tube to ensure that it is empty.

Do not massage the product into the skin. Due to alcohol content, do not apply to broken skin. Avoid contact between the product and fingers. Do not apply when the hair coat is wet. Stiff hair, clumping of hair, hair discoloration, or a slight powdery residue may be observed at the treatment site in some cats. These effects are temporary and do not affect the safety or effectiveness of the product. Discard empty tubes in your ordinary household refuse.

The effectiveness of REVOLUTION PLUS against D. immitis after bathing has not been evaluated. Bathing or shampooing the cat 24 hours after treatment does not reduce the effectiveness of topical selamectin, one of the ingredients of REVOLUTION PLUS, against D. immitis.

Flea Treatment and Prevention

For the treatment and prevention of flea infestations, REVOLUTION PLUS may begin at any time of year. REVOLUTION PLUS should be administered year-round at monthly intervals or begin at least one month before fleas become active. If a cat is already infested with fleas when the first dose of REVOLUTION PLUS is administered, adult fleas on the animal are killed before they can lay eggs. However, an environmental infestation may persist for a short time after beginning treatment with REVOLUTION PLUS because of the development of adult fleas from eggs that were laid prior to the initiation of treatment.

Tapeworm Prevention

For the prevention of Dipylidium caninum (tapeworm) infections as a direct result of killing Ctenocephalides felis vector fleas, REVOLUTION PLUS may begin at any time of year. REVOLUTION PLUS should be administered year-round at monthly intervals or begin at least one month before the fleas become active.
REVOLUTION PLUS will only prevent D. caninum infections by killing the fleas on the treated cat. Cats may also become infected with D. caninum by ingesting fleas from untreated animals, it is therefore recommended that all pets in a household are treated for fleas.

Tick Treatment and Control

For the treatment and control of infestations with Ixodes scapularis, Amblyomma maculatum, Dermacentor variabilis, and Amblyomma americanum, REVOLUTION PLUS may begin at any time of year. REVOLUTION PLUS should be administered year-round at monthly intervals or begin at least one month before the ticks become active.

Heartworm Prevention

For the prevention of heartworm disease, REVOLUTION PLUS must be administered on a monthly basis. REVOLUTION PLUS should be administered year-round or at least within one month after the animal’s first exposure to mosquitoes and monthly thereafter until the end of the mosquito season. The final dose must be given within one month after the last exposure to mosquitoes. If a dose is missed and a monthly interval between dosing is exceeded then immediate administration of REVOLUTION PLUS and resumption of monthly dosing will minimize the opportunity for the development of adult heartworms. When replacing another monthly heartworm preventive product in a heartworm disease prevention program, the first dose of REVOLUTION PLUS must be given within a month of the last dose of the former medication.

Selamectin, one of the active ingredients in REVOLUTION PLUS, is a macrocyclic lactone compound. These compounds effectively prevent the development of adult heartworms when administered to cats within one month of exposure to infective (L3) Dirofilaria immitis larvae. This product effectively eliminates the tissue stage of heartworm larvae for a month after infection. Cats with unknown heartworm history that test negative prior to the initiation of REVOLUTION PLUS may be harboring pre-patent infections at the time REVOLUTION PLUS was started. Testing such animals 3-4 months after initiation of REVOLUTION PLUS would be necessary to confirm their negative heartworm status.

At the discretion of the veterinarian, cats ≥ 6 months of age may be tested to determine the presence of existing heartworm infections before beginning treatment with REVOLUTION PLUS. Cats already infected with adult heartworms can be given REVOLUTION PLUS monthly to prevent further infections.

Ear Mite Treatment and Control

For the treatment of ear mite (Otodectes cynotis) infestations, REVOLUTION PLUS should be administered once as a single topical dose. Do not administer into the ear canal. Monthly use of REVOLUTION PLUS will control any subsequent ear mite infestations. Cleansing of the infested ears is recommended to remove debris.

Nematode Treatment and Control

For the treatment of roundworm (Toxocara cati) and intestinal hookworm (Ancylostoma tubaeforme) infections, REVOLUTION PLUS should be applied once as a single topical dose. Monthly use of REVOLUTION PLUS will control any subsequent roundworm and intestinal hookworm infections.

CONTRAINDICATIONS:

There are no known contraindications for the use of REVOLUTION PLUS.

WARNINGS:

Human warnings:

Not for human use. Keep this and all drugs out of the reach of children.

Do not come into contact with or allow children to contact the application site until 4 hours post application.

In humans, REVOLUTION PLUS may be irritating to skin and eyes. REVOLUTION PLUS and selamectin topical solution contain isopropyl alcohol and the preservative butylated hydroxytoluene (BHT). Reactions such as hives, itching and skin redness have been reported in humans after accidental dermal contact with selamectin topical solution. Individuals with known hypersensitivity to selamectin topical solution should use caution or consult a health care professional before applying this product on a cat. Wash hands after use and wash off any product in contact with the skin immediately with soap and water.
If contact with eyes occurs, then flush eyes copiously with water; if wearing contact lenses, rinse the eyes first then remove contact lenses and continue to rinse for 5 – 10 minutes and seek medical attention. In case of ingestion by a human, contact a physician immediately. The safety data sheet (SDS) provides more detailed occupational safety information. For a copy of the SDS or to report a suspected adverse reaction, call Zoetis at 1-888-963-8471.
Flammable - Keep away from heat, sparks, open flames or other sources of ignition.

PRECAUTIONS:

Sarolaner, one of the ingredients in REVOLUTION PLUS, is a member of the isoxazoline class. This class has been associated with neurologic adverse reactions including tremors, ataxia, and seizures. Neurologic adverse reactions have been reported in cats receiving isoxazoline class drugs, even in cats without a history of neurologic disorders. Use with caution in cats with a history of neurologic disorders.

The safe use of REVOLUTION PLUS has not been evaluated in kittens less than 8 weeks of age. The safe use of REVOLUTION PLUS has not been evaluated in breeding, pregnant, or lactating cats.

ADVERSE REACTIONS:

In a field safety and effectiveness study, REVOLUTION PLUS was administered to cats with fleas. The study included a total of 430 cats (282 treated with REVOLUTION PLUS and 148 treated with imidacloprid + moxidectin once monthly for three treatments). Over the 90-day study period, all observations of potential adverse reactions were recorded. Reactions reported in the REVOLUTION PLUS group included those presented in the following table.
Adverse Reactions by Treatment Group

Adverse Reaction | REVOLUTION PLUS (n = 282) | Imidacloprid + moxidectin (n =148)
Lethargy | 12 (4.3%) | 1 (0.7%)
Skin lesions* | 10 (3.5%) | 3 (2.0%)
Anorexia | 9 (3.2%) | 3 (2.0%)
Pruritus | 7 (2.5%) | 3 (2.0%)
Conjunctivitis | 7 (2.5%) | 1 (0.7%)
Sneezing | 6 (2.1%) | 1 (0.7%)
Administration site hair changes (alopecia) | 5 (1.8%) | 0 (0.0%)
Administration site lesions (scabbing) | 2 (0.7%) | 0 (0.0%)

*Lesions not associated with application site.
In a second field safety and effectiveness study, REVOLUTION PLUS was administered to 124 cats with ear mites. Adverse reactions in cats treated with REVOLUTION PLUS included emesis, dermatitis and eczema, and pruritus.

In a third field safety and effectiveness study, REVOLUTION PLUS was administered to 70 cats with hookworms. Adverse reactions in cats treated with REVOLUTION PLUS included diarrhea, anorexia, emesis, and lethargy.

Post-Approval Experience (2022)
The following adverse events are based on post-approval adverse drug experience reporting forREVOLUTION PLUS. Not all adverse events are reported to FDA/CVM. It is not always possible to reliably estimate the exposure using these data.
The following adverse events reported in cats are listed in decreasing order of reporting frequency:
Application site reactions (including alopecia, lesions, erythema, and pruritus), lethargy, anorexia, vomiting, generalized pruritus, behavioral disorders (including hiding, hyperactivity, and vocalization), ataxia, muscle tremor, diarrhea, generalized alopecia, and seizure.
Contact Information
To report adverse reactions call Zoetis Inc. at 1-888-963-8471. For additional information about adverse drug experience reporting for animal drugs, contact FDA at 1-888-FDA-VETS or http://www.fda.gov/reportanimalae.

CLINICAL PHARMACOLOGY:

Following topical administration of REVOLUTION PLUS both selamectin and sarolaner are well absorbed with mean absolute bioavailability of 40.5% and 57.9%, respectively, and distribute systemically. In cats, selamectin and sarolaner are low clearance compounds with a long half-life of 12.5 days and 41.5 days following topical administration, respectively. Following IV dose, the total body clearance for selamectin was 10.2 mL/kg/hr and for sarolaner was 3.41 mL/kg/hr. The volume of distribution at steady state was 1.26 L/kg for selamectin and 3.87 L/kg for sarolaner. The primary route of elimination for both drugs is hepatobiliary excretion (approximately 50% of dose excreted in feces).

Following repeated monthly doses of REVOLUTION PLUS, there was a less than dose proportional increase in the Cmax and AUC of sarolaner and selamectin. The accumulation of both sarolaner and selamectin was observed with Cmax plateauing after the 6th dose for sarolaner and the 3rd dose for selamectin.

MODE OF ACTION:

REVOLUTION PLUS contains two active pharmaceutical ingredients, selamectin and sarolaner. Selamectin is a semi-synthetic compound of the avermectin class. Selamectin paralyzes and/or kills a wide range of invertebrate parasites through interference with their chloride channel conductance causing disruption of normal neurotransmission. This inhibits the electrical activity of nerve cells in nematodes and muscle cells in arthropods leading to their paralysis and/or death. Sarolaner is an acaricide and insecticide belonging to the isoxazoline family. The primary target of action of sarolaner in insects and acarines is functional blockade of ligand-gated chloride channels (GABA-receptors and glutamate-receptors). Sarolaner blocks GABA- and glutamate-gated chloride channels in the nervous system of insects and acarines. Disruption of these receptors by sarolaner prevents the uptake of chloride ions by GABA and glutamate ion channels, thus resulting in increased nerve stimulation and death of the target parasite. Sarolaner exhibits higher functional potency to block insect/acarine receptors compared to mammalian receptors.

EFFECTIVENESS:

Flea Treatment and Prevention

In a well-controlled laboratory study, REVOLUTION PLUS started to kill fleas within 12 hours of treatment and killed >98% of fleas within 24 hours. During subsequent weekly infestations, REVOLUTION PLUS started to kill fleas within 6 hours and killed ≥93.8% of fleas within 12 hours through Day 28.
In a 90-day multi-center field study in the United States, conducted in households with existing flea infestations, the effectiveness of REVOLUTION PLUS against fleas was 97.2%, 99.5%, and 99.8% when assessed on Days 30, 60, and 90, respectively. Cats with signs of flea allergy dermatitis showed improvement in alopecia, dermatitis/pyodermatitis, pruritus, erythema, and papules, and scaling, as a direct result of eliminating fleas.
In two additional well-controlled laboratory studies, there was a 100% reduction in adult flea count against an existing infestation and weekly re-infestation for at least 35 days. In one of these studies in which flea egg laying was examined, no flea eggs were recovered from cats treated with REVOLUTION PLUS through Day 22, and on Day 36. Four flea eggs were recovered from one cat on Day 29, but none of these four eggs hatched and developed into adult fleas. Fleas on control cats continued to produce eggs throughout the study, with counts ranging from 110 - 1,256 eggs per cat.
Collectively, the data from the four studies (three laboratory and one field) demonstrate that REVOLUTION PLUS kills fleas before they can lay eggs, thus preventing further flea infestations from developing once treatment of the existing flea infestation has been initiated.

Tapeworm Prevention
In two well-controlled laboratory studies, a single topical dose of REVOLUTION PLUS was ≥ 97.1% effective in preventing Dipylidium caninum infections in cats after multiple infestations with Dipylidium caninum-infected C. felis fleas for one month.
Tick Treatment and Control

In well-controlled laboratory studies, REVOLUTION PLUS began to kill Ixodes scapularis ticks within 24 hours of administration and demonstrated ≥93.3% effectiveness 48 hours post re-infestation for a month. REVOLUTION PLUS demonstrated ≥91.6% effectiveness against Amblyomma maculatum 48 hours post-infestation for a month. At 72 hours post-infestation, REVOLUTION PLUS demonstrated ≥93.5% effectiveness against Dermacentor variabilis and ≥92.5% effectiveness against Amblyomma americanum for a month.
Heartworm Prevention

In two well-controlled laboratory studies, a single topical dose of REVOLUTION PLUS was 100% effective in preventing the development of heartworms in cats inoculated with infective larvae of Dirofilaria immitis 30 days prior to treatment.
Ear Mite Treatment and Control

In a well-controlled laboratory study, a single topical dose of REVOLUTION PLUS resulted in > 99% effectiveness against an existing Otodectes cynotis infestation at 30 days post treatment. In a multi-center field study conducted in households with existing Otodectes cynotis infestations, 94.4% of cats in the group treated with REVOLUTION PLUS were negative for ear mites at Day 30.
Nematode Treatment and Control

Elimination of intestinal hookworm (Ancylostoma tubaeforme) and roundworm (Toxocara cati) infections was demonstrated in well-controlled laboratory studies.

In a 60-day multi-center field study, the effectiveness of REVOLUTION PLUS in reducing Ancylostoma tubaeforme fecal egg counts was 99.4% and 99.7% on Days 30 and 60, respectively.

ANIMAL SAFETY:

Margin of Safety Studies: One exploratory and two pivotal margin of safety studies were conducted with REVOLUTION PLUS. In the first study, REVOLUTION PLUS was applied topically to kittens eight weeks of age at doses of 12/2 (selamectin/sarolaner) mg/kg (1X), 36/6 mg/kg (3X), 45/7.5 mg/kg (3.75X), and 60/10 mg/kg (5X) every 28 days for eight consecutive doses. One female cat in the 3.75X group was found dead on study day 115. The cause was determined to be hemorrhage in multiple tissues secondary to a low platelet count. The role of the drug in contributing to this event is undetermined. No significant changes related to REVOLUTION PLUS were observed among the remaining cats for physical examination, body weight, clinical pathology (hematology, coagulation, and serum chemistry), gross pathology, histopathology or organ weights.

In the second study, REVOLUTION PLUS was applied topically to cats 9 months of age at doses of 1X, 3X, and 5X every 28 days for six consecutive doses. Cosmetic changes at the application site occurred sporadically in all treatment groups and included wet appearance and dried white material. Hair loss at the dose site was also noted in two cats in the 1X group and one cat in the 5X group within 1-8 days after the fourth dose administered on day 84. No significant changes related to REVOLUTION PLUS were observed for physical examination, body weight, clinical pathology (hematology, coagulation, and serum chemistry).

During an exploratory margin of safety study, one cat in the 60 mg/kg/ 10 mg/kg (selamectin/sarolaner) group (5X dose group) experienced piloerection, tremors, and mydriasis approximately 24 hours after receiving the third monthly dose of the combination. Signs resolved without treatment within 2 hours. This cat completed the study, receiving 3 subsequent 5X doses with no abnormal observations.

Oral safety study: The safety of REVOLUTION PLUS administered orally to kittens was tested in case of accidental oral ingestion. Oral administration of the highest recommended topical dose of REVOLUTION PLUS to kittens resulted in transient lower food consumption and clinical findings of emesis, soft feces, and salivation. In one male, mild tremor was observed and resolved within 3 hours after dosing; the same cat demonstrated reduced activity approximately 6 hours after dosing.

Heartworm Positive Cat Safety of Selamectin: Selamectin is the active ingredient in REVOLUTION PLUS that prevents heartworm disease in cats; it has been shown that the addition of sarolaner does not interfere with this activity. In a safety study in which selamectin topical solution was applied at 4 times the recommended dose to patent heartworm infected cats, no adverse reactions were observed.

Field safety: In three well-controlled field studies, REVOLUTION PLUS was used concurrently with other medications, such as vaccines, cestocidal anthelmintics, antibacterials, sedatives, anesthetics, opioid analgesics, corticosteroids, and non-steroidal anti-inflammatories. No adverse reactions were associated with the concurrent use of REVOLUTION PLUS and other medications.

STORAGE CONDITIONS:

Store at or below 30°C (86°F).

HOW SUPPLIED:

Available in three separate dose strengths for cats of different weights (see DOSAGE AND ADMINISTRATION). REVOLUTION PLUS is available in cartons containing one, three, or six single dose tubes. The amount of liquid in tube varies for each weight range (2.8 - 5.5 lbs, 5.6 - 11 lbs, 11.1- 22 lbs).
Tubes are never completely filled.

Approved by FDA under NADA # 141-502
Revised: October 2024
zoetis
Distributed by:
Zoetis Inc.
Kalamazoo, MI 49007
51859500

PRINCIPAL DISPLAY PANEL - 0.25 3-pack Carton

40046217

PRINCIPAL DISPLAY PANEL - 0.5 3-pack Carton

40046218

PRINCIPAL DISPLAY PANEL - 1 mL 3-pack Carton

40046222